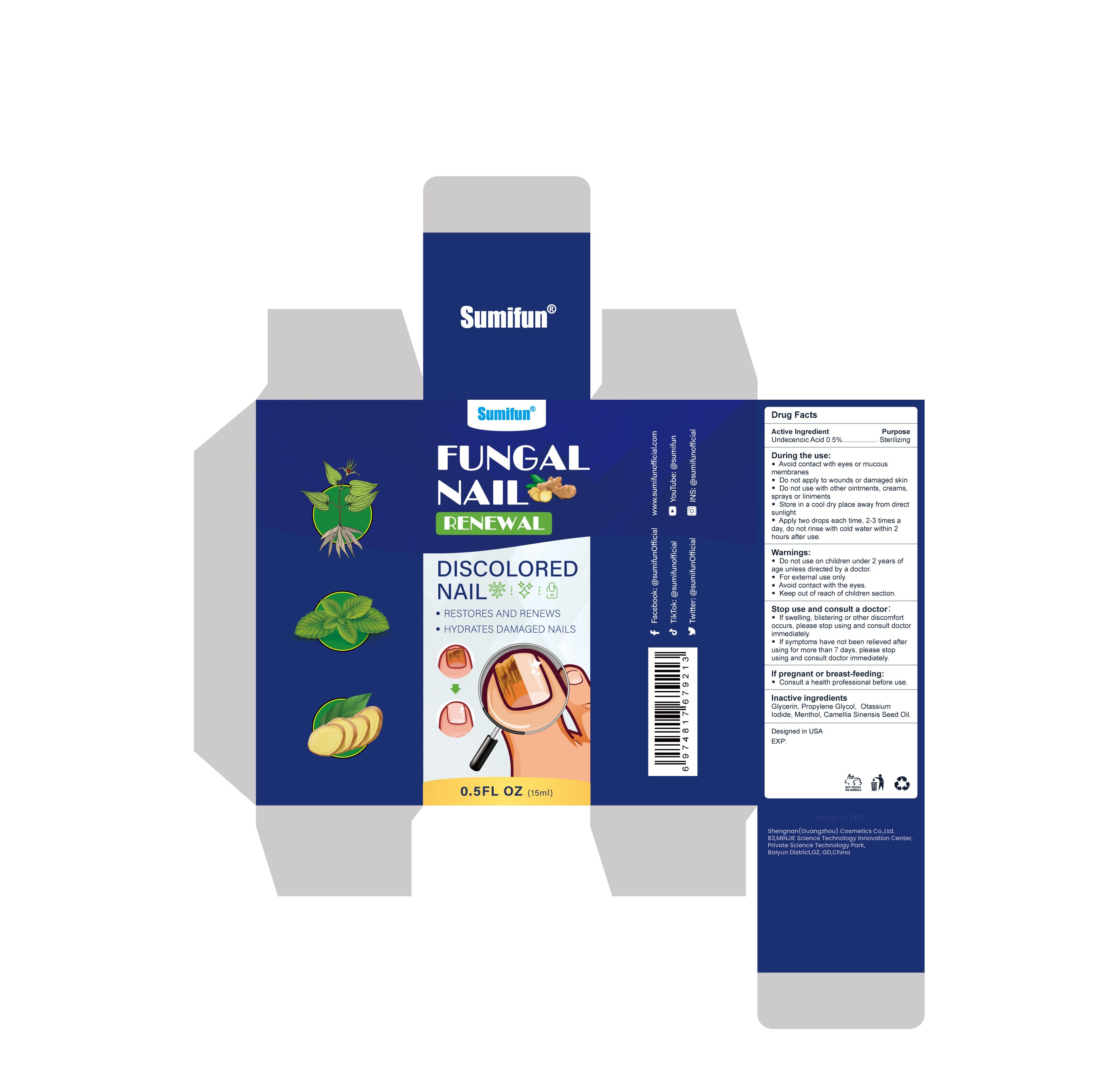 DRUG LABEL: Fungal Nail Renewal
NDC: 84019-201 | Form: LIQUID
Manufacturer: Shengnan (Guangzhou) Cosmetics Co., LTD
Category: otc | Type: HUMAN OTC DRUG LABEL
Date: 20240124

ACTIVE INGREDIENTS: 11-HYDROXY-2-UNDECENOIC ACID 0.005 g/1 mL
INACTIVE INGREDIENTS: POTASSIUM IODIDE; METAHOMOMENTHOL, (+/-)-; CAMELLIA SINENSIS SEED OIL; GLYCERIN; PROPYLENE GLYCOL

Fungal Nail Renewal

Fungal Nail Renewal

ACTIVE INGREDIENT

Undecenoic Acid 0.5%

PURPOSE

Sterilizing

INDICATIONS AND USAGE

RESTORES AND RENEWS
HYDRATES DAMAGED NAILS

Do not use on children under 2 years of age unless directed by a doctor.
For external use only.
Avoid contact with the eyes.
Keep out of reach of children section.

Do not use on children under 2 years of age unless directed by a doctor.

WHEN USING

Avoid contact with eyes or mucous membranes.
Do not apply to wounds or damaged skin.
Do not use with other ointments, creams, sprays or liniments.

STOP USE

If swelling, blistering or other discomfort occurs,please stop using and consult doctor immediately.
If symptoms have not been relieved after using for more than 7 days, please stop using and consult doctor immediately.

Keep out of reach of children section.

DOSAGE AND ADMINISTRATION

Apply two drops each time, 2-3 times a day, do not rinse with cold water within 2 hours after use.

STORAGE AND HANDLING

Store in a cool dry place away from direct sunlight.

INACTIVE INGREDIENT

Glycerin
Propylene Glycol
Otassium Iodide
Menthol
Camellia Sinensis Seed Oil